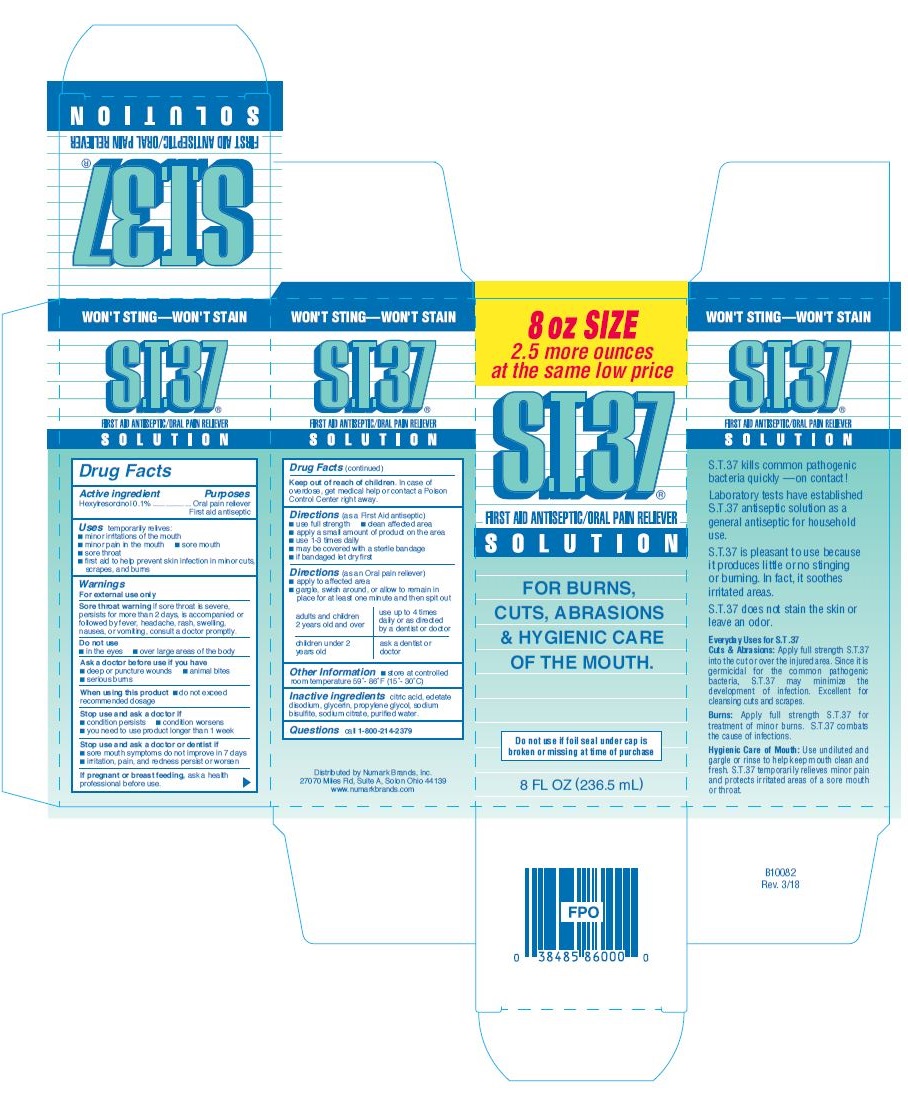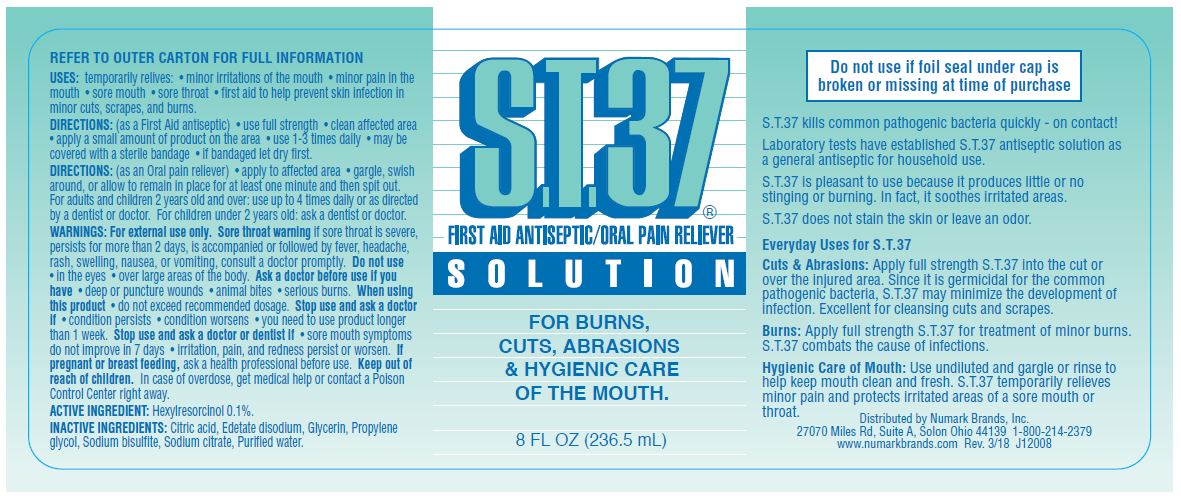 DRUG LABEL: S.T.37
NDC: 69846-860 | Form: SOLUTION
Manufacturer: NUMARK BRANDS, INC
Category: otc | Type: HUMAN OTC DRUG LABEL
Date: 20251215

ACTIVE INGREDIENTS: Hexylresorcinol 1.1 mg/1 mL
INACTIVE INGREDIENTS: Citric Acid Monohydrate; Edetate Disodium; Glycerin; Propylene Glycol; Sodium Bisulfite; Sodium Citrate; Water

Drug Facts

ACTIVE INGREDIENT

Active Ingredient | Purposes
Hexylresorinol 0.1% | Oral Pain Reliever
 | First aid antiseptic

INDICATIONS AND USAGE

Uses temporarily relieves:

- minor irritations of the mouth
- minor pain in the mouth
- sore mouth
- sore throat
- first aid to help prevent skin infection in minor cuts, scrapes, and burns

Warnings

For external use only

WARNINGS AND PRECAUTIONS

Sore throat warning if sore throat is severe, persists for more than 2 days, is accompanied or followed by fever, headache, rash, swelling, nausea, or vomiting, consult a doctor promptly.

Do not use

- In the eyes
- over large areas of the body

Ask a doctor before use if you have

- deep or puncture wounds
- animal bites
- serious burns

When using this product

- do not exceed recommended dosage

Stop use and ask a doctor if

- condition persists
- condition worsens
- you need to use product longer than 1 week

Stop use and ask a doctor or dentist if

- sore mouth symptoms do not improve in 7 days
- irritation, pain, and redness persist or worsen

PREGNANCY OR BREAST FEEDING

If pregnant or breast feeding, ask a health professional before use.

Keep out of reach of children. In case of overdose, get medical help or contact a Poison Control Center right away.

DOSAGE AND ADMINISTRATION

Directions (as a First Aid antiseptic)

- use full strength
- clean affected area
- apply a small amount of product on the area
- use 1-3 times daily
- may be covered with a sterile bandage
- if bandaged let dry first

DOSAGE AND ADMINISTRATION

Directions (as an Oral pain reliever)

- apply to affected area
- gargle, swish around, or allow to remain in place for at least one minute and then spit out

adults and children 2 years old and over | use up to 4 times daily or as directed by a dentist or doctor
children under 2 years old | ask a dentist or doctor

Other Information

- store at controlled room temperature 59° - 86°F (15° - 30°C)

Inactive Ingredients

citric acid, edetate disodium, glycerin, propylene glycol, sodium bisulfite, sodium citrate, purified water.

Questions call 1-800-214-2379

PACKAGE LABEL.PRINCIPAL DISPLAY PANEL

8 oz SIZE
2.5 more ounces at the same low price
S.T.37®
FIRST AID ANTISEPTIC/ORAL PAIN RELIEVER
SOLUTION
FOR BURNS, CUTS, ABRASIONS & HYGIENIC CARE OF THE MOUTH.
Do not use if foil seal under cap is broken or missing at time of purchase
8 FL OZ (236.5 mL)
WON'T STING — WON'T STAIN
S.T.37 kills common pathogenic bacteria quickly — on contact!
Laboratory tests have established S.T.37 antiseptic solution as a general antiseptic for household use.
S.T.37 is pleasant to use because it produces little or no stinging or burning. In fact, it soothes irritated areas.
S.T.37 does not stain the skin or leave an order.
Everyday Uses for S.T.37
Cuts & Abrasions: Apply full strength S.T.37 into the cut or over the injured area. Since it is germicidal for the common pathogenic bacteria, S.T.37 may minimize the development of infection. Excellent for cleansing cuts and scrapes.
Burns: Apply full strength S.T.37 for treatment of minor burns. S.T.37 combats the cause of infections.
Hygienic Care of Mouth: Use undiluted and gargle or rinse to help keep mouth clean and fresh. S.T.37 temporarily relieves minor pain and protects irritated areas of a sore mouth or throat.
Distributed by Numark Brands, Inc.
27070 Miles Rd, Suite A, Solon Ohio 44139
www.numarkbrands.com
B10082
Rev. 3/18

S.T.37®
FIRST AID ANTISEPTIC/ORAL PAIN RELIEVER
SOLUTION
FOR BURNS, CUTS, ABRASIONS & HYGIENIC CARE OF THE MOUTH
8 FL OZ (236.5 mL)
Do not use if foil seal under cap is broken or missing at time of purchase
S.T.37 kills common pathogenic bacteria quickly - on contact!
Laboratory tests have established S.T.37 antiseptic solution as a general antiseptic for household use.
S.T.37 is pleasant to use because it produces little or no stinging or burning. In fact, it soothes irritated areas.
S.T.37 does not stain the skin or leave an order.
Everyday Uses for S.T.37
Cuts & Abrasions: Apply full strength S.T.37 into the cut or over the injured area. Since it is germicidal for the common pathogenic bacteria, S.T.37 may minimize the development of infection. Excellent for cleansing cuts and scrapes.
Burns: Apply full strength S.T.37 for treatment of minor burns. S.T.37 combats the cause of infections.
Hygienic Care of Mouth: Use undiluted and gargle or rinse to help keep mouth clean and fresh. S.T.37 temporarily relieves minor pain and protects irritated areas of a sore mouth or throat.
Distributed by Numark Brands, Inc.
27070 Miles Rd, Suite A, Solon Ohio 44139 1-800-214-2379
www.numarkbrands.com Rev. 3/18 J12008